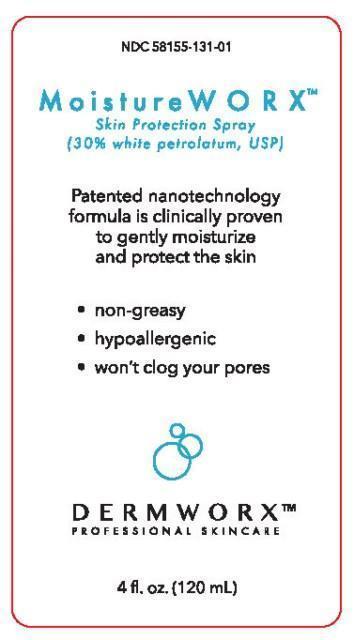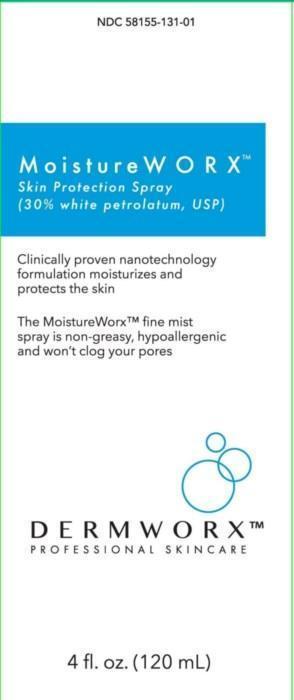 DRUG LABEL: MoistureWorx
NDC: 58155-131 | Form: SPRAY
Manufacturer: Juventio LLC
Category: otc | Type: HUMAN OTC DRUG LABEL
Date: 20140811

ACTIVE INGREDIENTS: PETROLATUM 36 g/120 mL
INACTIVE INGREDIENTS: GLYCERYL DISTEARATE; STEARETH-10; CHOLESTEROL; SODIUM LAURETH SULFATE; POLYSORBATE 80; PROPYLENE GLYCOL; METHYLPARABEN; DIAZOLIDINYL UREA; PROPYLPARABEN

MoistureWORX™ Skin Protection Spray
(30% White Petrolatum, USP)

Drug Facts

Active Ingredient

White Petrolatum, USP 30%

Purpose

Skin Protectant Spray

Use

- Temporarily protects chapped or cracked skin
- Helps protect from the drying effects of wind and cold weather

Warnings

For external use only

When using this product

- do not get into eyes

See a doctor if

- condition lasts more than 7 days.

Do not use on

- deep or puncture wounds
- animal bites
- serious burns

Keep out of reach of children. If swallowed get medical help or contact a Poison Control Center immediately.

Directions

- apply as needed

Inactive Ingredients

Water, Glyceryl Distearate, Steareth-10, Cholesterol, Sodium Laureth Sulfate, Polysorbate 80, Propylene Glycol, Methylparaben, Diazolidinyl Urea, Propylparaben

Principal Display Panel - Bottle Label

NDC 58155-131-01

MoistureWORX™

Skin Protection Spray

(30% white petrolatum, USP)

Patented nanotechnology formula is clinically proven to gently moisturize and protect the skin

- non-greasy
- hypoallergenic
- won't clog your pores

DERMWORX™

PROFESSIONAL SKINCARE

4 fl. oz. (120 mL)

Principal Display Panel - Carton Label

NDC 58155-131-01

MositureWORX™

Skin Protection Spray

(30% white petrolatum, USP)

Clinically proven nanotechnology formulation moisturizes and protects the skin

The MoistureWorx™ fine mist spray is non-greasy, hypoallergenic and won't clog your pores

DERMWORX™

PROFESSIONAL SKINCARE

4 fl. oz. (120 mL)